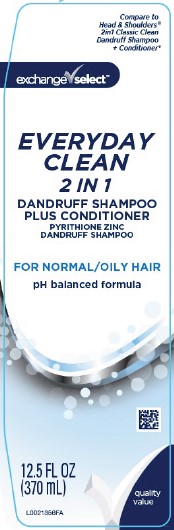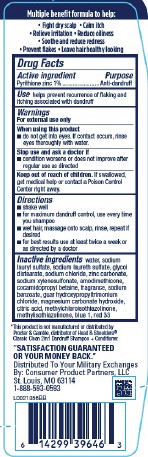 DRUG LABEL: Everyday Clean 2 in 1
NDC: 55301-311 | Form: SHAMPOO
Manufacturer: Your Military Exchanges
Category: otc | Type: HUMAN OTC DRUG LABEL
Date: 20260212

ACTIVE INGREDIENTS: PYRITHIONE ZINC 10 mg/10 mL
INACTIVE INGREDIENTS: WATER; SODIUM LAURYL SULFATE; SODIUM LAURETH SULFATE; GLYCOL DISTEARATE; SODIUM CHLORIDE; ZINC CARBONATE; SODIUM XYLENESULFONATE; AMODIMETHICONE (800 CST); COCAMIDOPROPYL BETAINE; SODIUM BENZOATE; GUAR HYDROXYPROPYLTRIMONIUM CHLORIDE (1.7 SUBSTITUENTS PER SACCHARIDE); MAGNESIUM CARBONATE HYDROXIDE; CITRIC ACID MONOHYDRATE; METHYLCHLOROISOTHIAZOLINONE; METHYLISOTHIAZOLINONE; FD&C BLUE NO. 1; D&C RED NO. 33

Exchange Select 311.007/311 AK-AN
Everyday Clean 2 in 1 Dandruff Shampoo

Claims

Multiple benefit formula to help:

- Fight dry scalp
- Calm itch
- Relieve irritation
- Reduce oiliness
- Soothe and reduce redness
- Prevent flakes
- Leave hair healthy looking

Active ingredient

Pyrithione zinc 1%

Purpose

Anti-dandruff

Use

Helps prevent recurrence of flaking and itching associated with dandruff

Warnings

For external use only

When using this product

- do not get into eyes. If contact occurs, rinse eyes thoroughly with water.

Stop use and ask a doctor if

- condition worsens or does not improve after regular use as directed

Keep out of reach of children.

If swallowed, get medical help or contact a Poison Control Center right away.

Directions

- shake well
- for maximum dandruff control, use every time you shampoo
- wet hair, massage onto scalp, rinse, repeat if desired
- for best results use at least twice a week or as directed by a doctor

inactive ingredients

water, sodium lauryl sulfate, sodium laureth sulfate, glycol distearate, sodium chloride, zinc carbonate, sodium xylenesulfonate, amodimethicone, cocamidopropyl betaine, fragrance, sodium benzoate, guar hydroxypropyltrimonium chloride, magnesium carbonate hydroxide, citric acid, methylchloroisothiazolinone, methylisothiazolinone, blue 1, red 33

Disclaimer

*This product is not manufactured or distributed by Procter & Gamble, the distributor of Head & Shoulders® Classic Clean 2 in 1 Dandruff Shampoo + Conditioner.

Adverse Reaction

"SATISFACTION GUARANTEED OR YOUR MONEY BACK."

Distributed To Your Military Exchanges

By: Consumer Product Partners, LLC

St. Louis, MO 63114

1-888-593-0593

Principal display panel

Compare to Head & Shoulders®2 in 1 Classic Clean Dandruff Shampoo + Conditioner.*

exchange select™

EVERYDAY CLEAN

2 IN 1

DANDRUFF SHAMPOO

PLUS CONDITIONER

PYRITHIONE ZINC

DANDRUFF SHAMPOO

FOR NORMAL/OILY HAIR

pH balanced formula

quality value

12.5 FL OZ (370 mL)